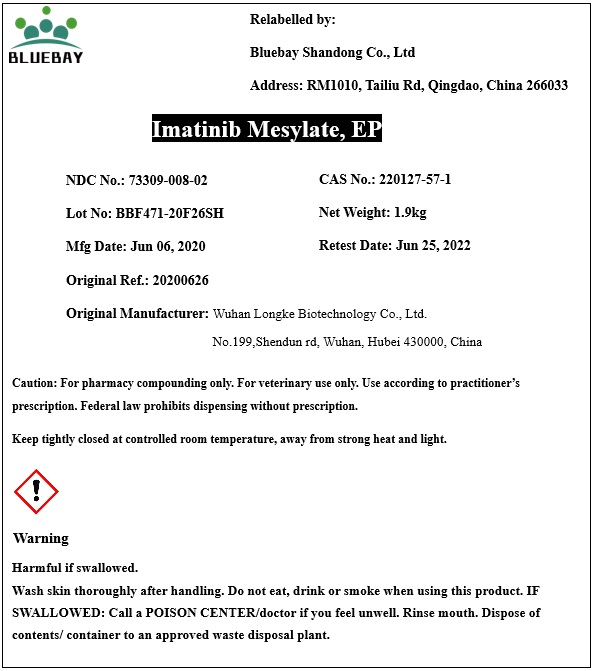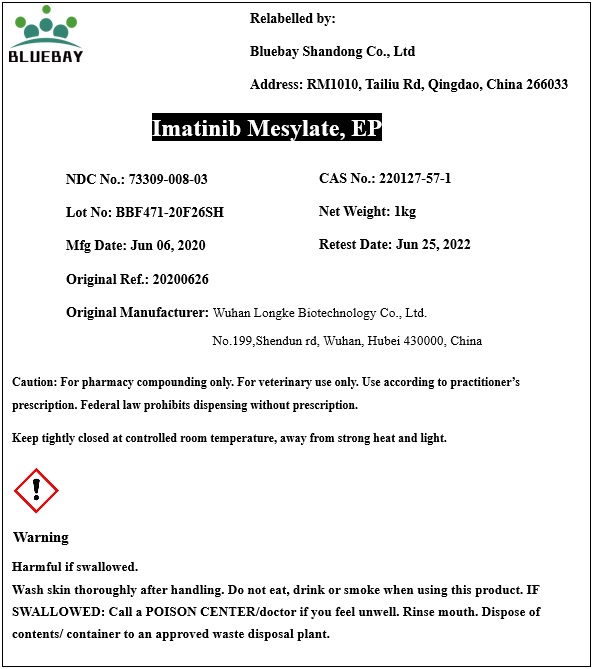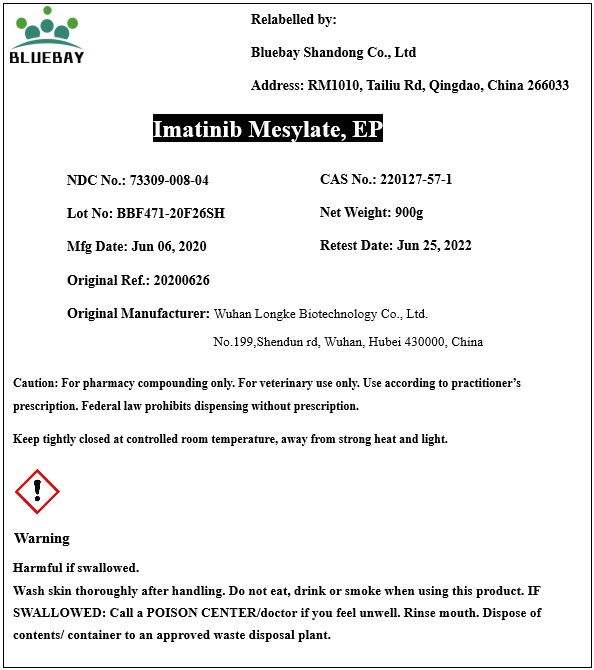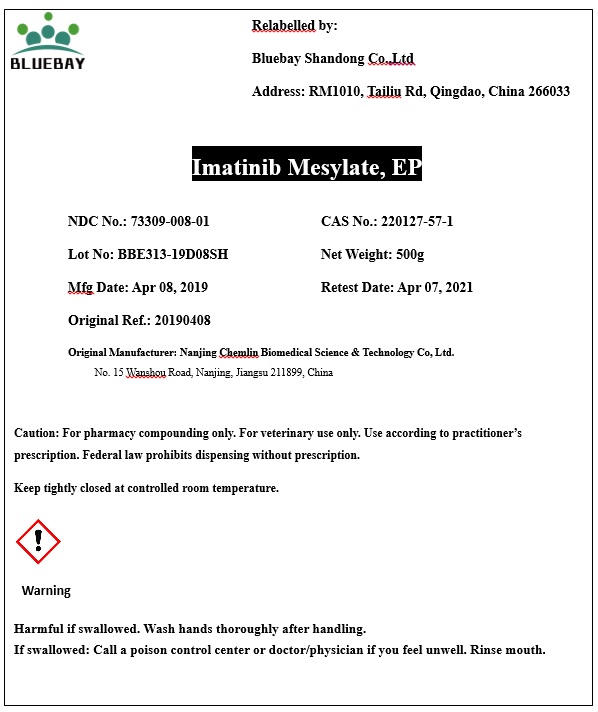 DRUG LABEL: Imatinib Mesylate
NDC: 73309-008 | Form: POWDER
Manufacturer: BLUEBAY SHANDONG CO.,LTD
Category: other | Type: BULK INGREDIENT
Date: 20201202

ACTIVE INGREDIENTS: IMATINIB MESYLATE 1 g/1 g

Imatinib Mesylate